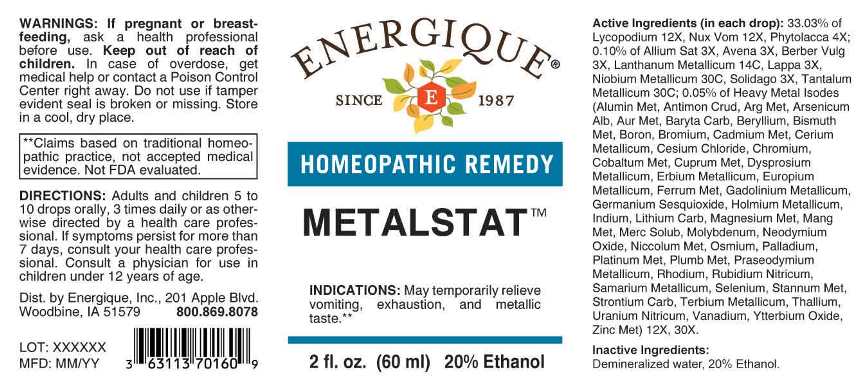 DRUG LABEL: Metalstat
NDC: 44911-0650 | Form: LIQUID
Manufacturer: Energique, Inc.
Category: homeopathic | Type: HUMAN OTC DRUG LABEL
Date: 20241029

ACTIVE INGREDIENTS: GARLIC 3 [hp_X]/1 mL; AVENA SATIVA FLOWERING TOP 3 [hp_X]/1 mL; BERBERIS VULGARIS ROOT BARK 3 [hp_X]/1 mL; ARCTIUM LAPPA ROOT 3 [hp_X]/1 mL; SOLIDAGO VIRGAUREA FLOWERING TOP 3 [hp_X]/1 mL; PHYTOLACCA AMERICANA ROOT 4 [hp_X]/1 mL; LYCOPODIUM CLAVATUM SPORE 12 [hp_X]/1 mL; STRYCHNOS NUX-VOMICA SEED 12 [hp_X]/1 mL; LANTHANUM 14 [hp_C]/1 mL; NIOBIUM 30 [hp_C]/1 mL; TANTALUM 30 [hp_C]/1 mL; ALUMINUM 12 [hp_X]/1 mL; ANTIMONY TRISULFIDE 12 [hp_X]/1 mL; SILVER 12 [hp_X]/1 mL; ARSENIC TRIOXIDE 12 [hp_X]/1 mL; GOLD 12 [hp_X]/1 mL; BARIUM CARBONATE 12 [hp_X]/1 mL; BERYLLIUM 12 [hp_X]/1 mL; BISMUTH 12 [hp_X]/1 mL; BORON 12 [hp_X]/1 mL; BROMINE 12 [hp_X]/1 mL; CADMIUM 12 [hp_X]/1 mL; CERIUM 12 [hp_X]/1 mL; CESIUM CHLORIDE 12 [hp_X]/1 mL; CHROMIUM 12 [hp_X]/1 mL; COBALT 12 [hp_X]/1 mL; COPPER 12 [hp_X]/1 mL; DYSPROSIUM 12 [hp_X]/1 mL; ERBIUM 12 [hp_X]/1 mL; EUROPIUM OXIDE 12 [hp_X]/1 mL; IRON 12 [hp_X]/1 mL; GADOLINIUM OXIDE 12 [hp_X]/1 mL; GERMANIUM SESQUIOXIDE 12 [hp_X]/1 mL; HOLMIUM 12 [hp_X]/1 mL; INDIUM 12 [hp_X]/1 mL; LITHIUM CARBONATE 12 [hp_X]/1 mL; MAGNESIUM 12 [hp_X]/1 mL; MANGANESE 12 [hp_X]/1 mL; MERCURIUS SOLUBILIS 12 [hp_X]/1 mL; MOLYBDENUM 12 [hp_X]/1 mL; NEODYMIUM OXIDE 12 [hp_X]/1 mL; NICKEL 12 [hp_X]/1 mL; OSMIUM 12 [hp_X]/1 mL; PALLADIUM 12 [hp_X]/1 mL; PLATINUM 12 [hp_X]/1 mL; LEAD 12 [hp_X]/1 mL; PRASEODYMIUM 12 [hp_X]/1 mL; RHODIUM 12 [hp_X]/1 mL; RUBIDIUM NITRITE 12 [hp_X]/1 mL; SAMARIUM OXIDE 12 [hp_X]/1 mL; SELENIUM 12 [hp_X]/1 mL; TIN 12 [hp_X]/1 mL; STRONTIUM CARBONATE 12 [hp_X]/1 mL; TERBIUM 12 [hp_X]/1 mL; THALLIUM 12 [hp_X]/1 mL; URANYL NITRATE HEXAHYDRATE 12 [hp_X]/1 mL; VANADIUM 12 [hp_X]/1 mL; YTTERBIUM OXIDE 12 [hp_X]/1 mL; ZINC 12 [hp_X]/1 mL
INACTIVE INGREDIENTS: WATER; ALCOHOL

DRUG FACTS:

ACTIVE INGREDIENTS:

(in each drop): 33.03% of Lycopodium Clavatum 12X, Nux Vomica 12X, Phytolacca Decandra 4X; 0.10% of Allium Sativum 3X, Avena Sativa 3X, Berberis Vulgaris 3X, Lanthanum Metallicum 14C, Lappa Major 3X, Niobium Metallicum 30C, Solidago Virgaurea 3X, Tantalum Metallicum 30C; 0.05% of Aluminium Metallicum 12X, 30X, Antimonium Crudum 12X, 30X, Argentum Metallicum 12X, 30X, Arsenicum Album 12X, 30X, Aurum Metallicum 12X, 30X, Baryta Carbonica 12X, 30X, Beryllium Metallicum 12X, 30X, Bismuthum Metallicum 12X, 30X, Boron 12X, 30X, Bromium 12X, 30X, Cadmium Metallicum 12X, 30X, Cerium Metallicum 12X, 30X, Cesium Chloride 12X, 30X, Chromium 12X, 30X, Cobaltum Metallicum 12X, 30X, Cuprum Metallicum 12X, 30X, Dysprosium Metallicum 12X, 30X, Erbium Metallicum 12X, 30X, Europium Metallicum 12X, 30X, Ferrum Metallicum 12X, 30X, Gadolinium Metallicum 12X, 30X, Germanium Sesquioxide 12X, 30X, Holmium Metallicum 12X, 30X, Indium Metallicum 12X, 30X, Lithium Carbonicum 12X, 30X, Magnesium Metallicum 12X, 30X, Manganum Metallicum 12X, 30X, Mercurius Solubilis 12X, 30X, Molybdenum 12X, 30X, Neodymium Oxide 12X, 30X, Niccolum Metallicum 12X, 30X, Osmium Metallicum 12X, 30X, Palladium Metallicum 12X, 30X, Platinum Metallicum 12X, 30X, Plumbum Metallicum 12X, 30X, Praseodymium Metallicum 12X, 30X, Rhodium Metallicum 12X, 30X, Rubidium Nitricum 12X, 30X, Samarium Metallicum 12X, 30X, Selenium Metallicum 12X, 30X, Stannum Metallicum 12X, 30X, Strontium Carbonicum 12X, 30X, Terbium Metallicum 12X, 30X, Thallium Metallicum 12X, 30X, Uranium Nitricum 12X, 30X, Vanadium Metallicum 12X, 30X, Ytterbium Oxide 12X, 30X, Zincum Metallicum 12X, 30X.

INDICATIONS:

May temporarily relieve vomiting, exhaustion, and metallic taste.**

**Claims based on traditional homeopathic practice, not accepted medical evidence. Not FDA evaluated.

WARNINGS:

If pregnant or breast-feeding, ask a health professional before use.

Keep out of reach of children. In case of overdose, get medical help or contact a Poison Control Center right away.

Do not use if tamper evident seal is broken or missing. Store in a cool, dry place.

Keep out of reach of children. In case of overdose, get medical help or contact a Poison Control Center right away.

DIRECTIONS:

Adults and children 5 to 10 drops orally, 3 time daily or as otherwise directed by a health care professional. If symptoms persist for more than 7 days, consult your health care professional. Consult a physician for use in children under 12 years of age.

INDICATIONS:

May temporarily relieve vomiting, exhaustion, and metallic taste.**

**Claims based on traditional homeopathic practice, not accepted medical evidence. Not FDA evaluated.

INACTIVE INGREDIENTS:

Demineralized water, 20% Ethanol.

QUESTIONS:

Dist. by Energique, Inc.

201 Apple Blvd

Woodbine, IA 51579 800-869-8078

PACKAGE LABEL DISPLAY:

ENERGIQUE

SINCE 1987

HOMEOPATHIC REMEDY

METALSTAT

2 fl. oz. (60 ml)